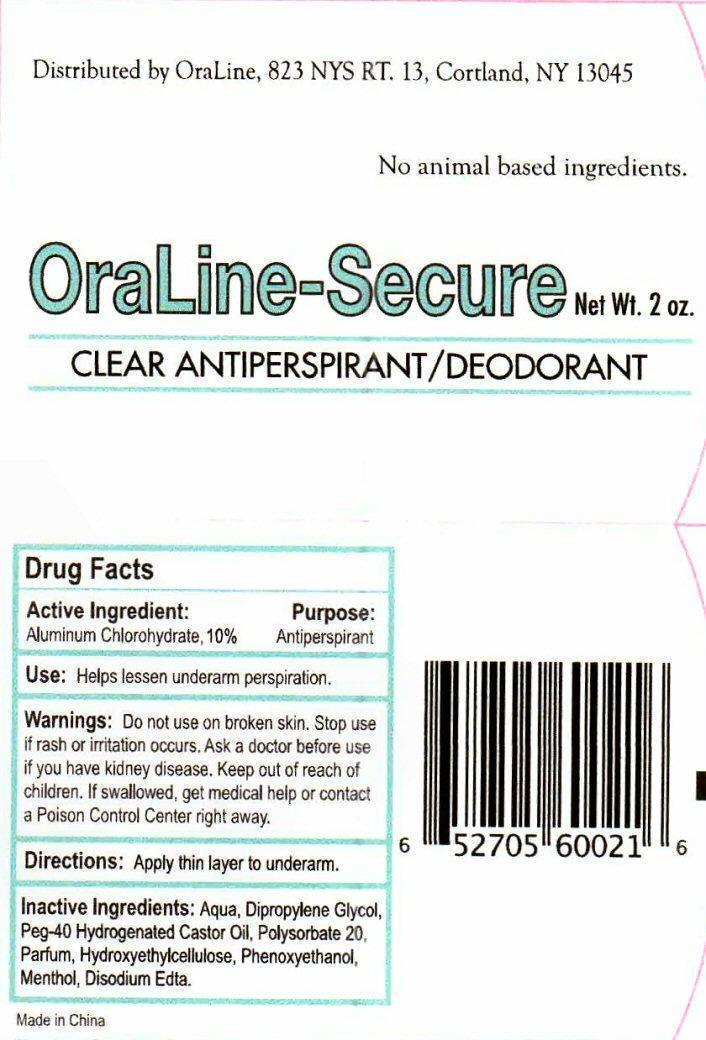 DRUG LABEL: OraLine-Secure
NDC: 55873-021 | Form: GEL
Manufacturer: J.M. Murray Center Inc.
Category: otc | Type: HUMAN OTC DRUG LABEL
Date: 20190120

ACTIVE INGREDIENTS: ALUMINUM CHLOROHYDRATE 5.67 g/56.7 g
INACTIVE INGREDIENTS: WATER; DIPROPYLENE GLYCOL; POLYOXYL 40 HYDROGENATED CASTOR OIL; POLYSORBATE 20; HYDROXYETHYL CELLULOSE (2000 MPA.S AT 1%); PHENOXYETHANOL; MENTHOL; EDETATE DISODIUM

Active Ingredient:

Drug Facts

Active Ingredient:

Aluminum Chlorohydrate, 10%

Purpose:

Antiperspirant

Keep out of reach of children. If swallowed, get medical help or contact a Poison Control Center right away.

Use:

Helps lessen underarm perspiration.

Warnings:

Do not use on broken skin. Stop use if rash or irritation occurs. Ask a doctor before use if you have kidney disease.

Directions:

Apply thin layer to underarm.

Inactive Ingredients:

Aqua, Dipropylene Glycol, Peg-40 Hydrogenated Castor Oil, Polysorbate 20, Parfum, Hydroxyethylcellulose, Phenoxyethanol, Menthol, Disodium Edta.

Product Label

Distributed by OraLine, 823 NYS RT. 13, Cortland, NY 13045

No animal based ingredients.

Ora-Line Secure net Wt. 2 oz.

CLEAR ANTIPERSPIRANT/DEODORANT

Made in China

res